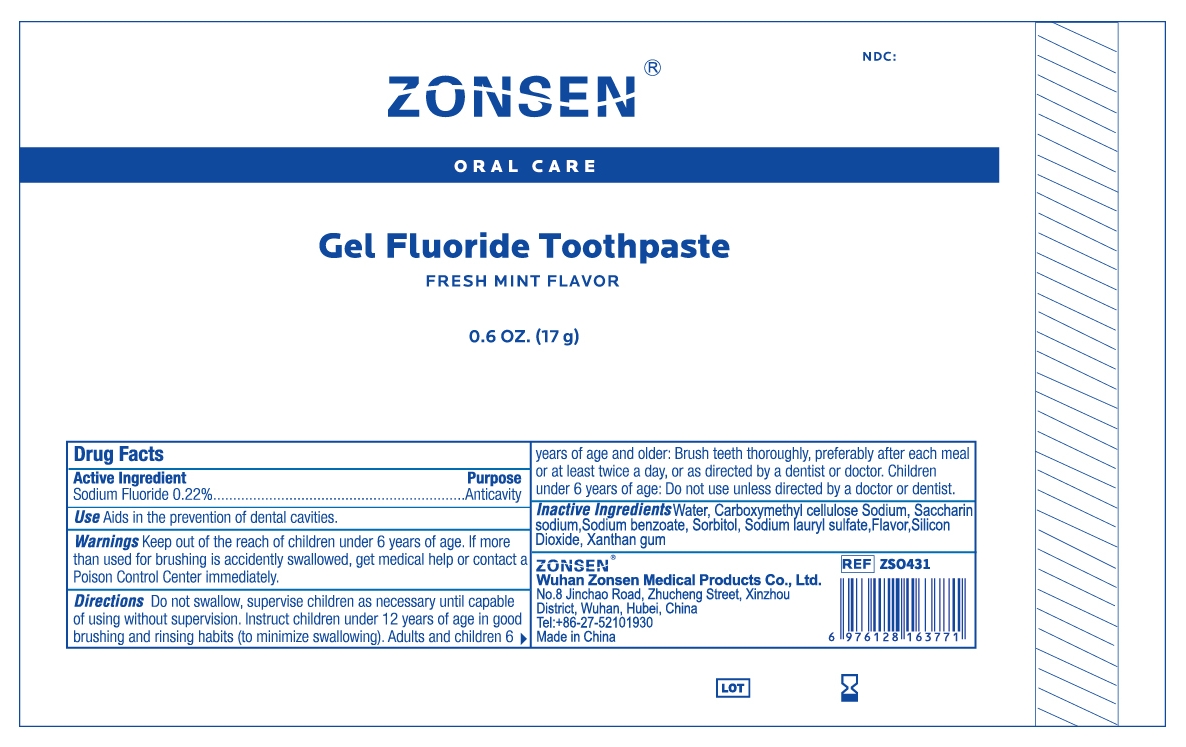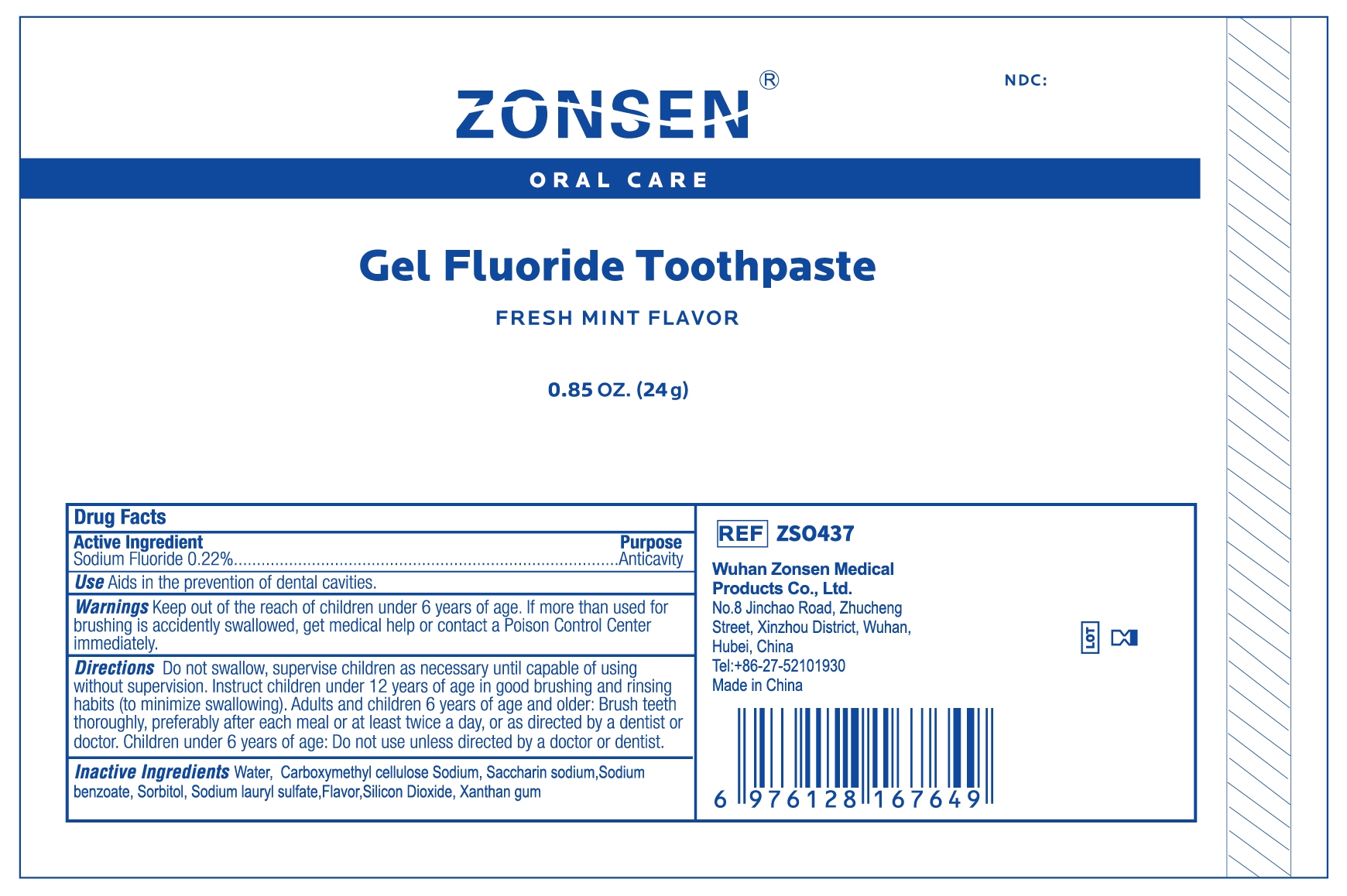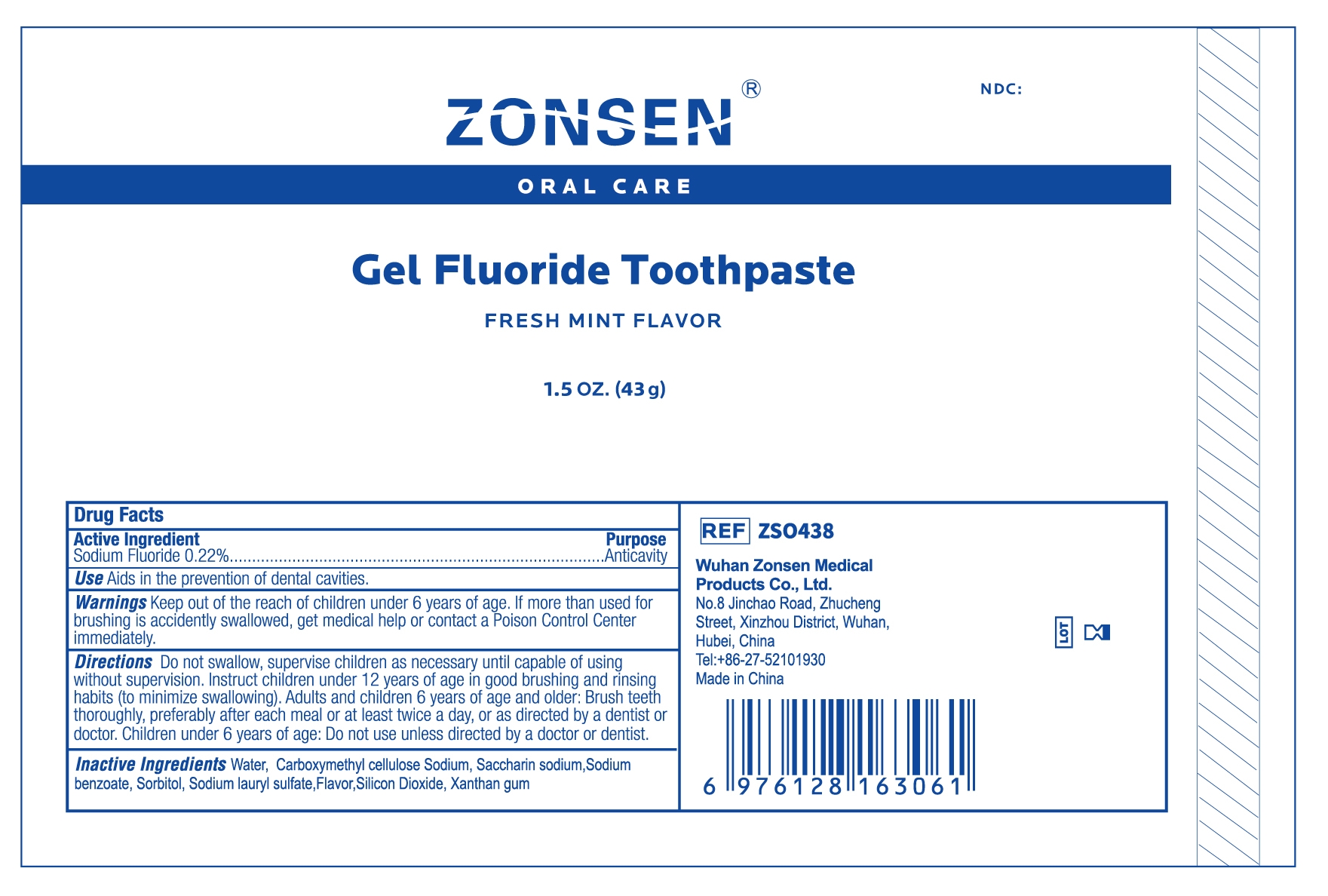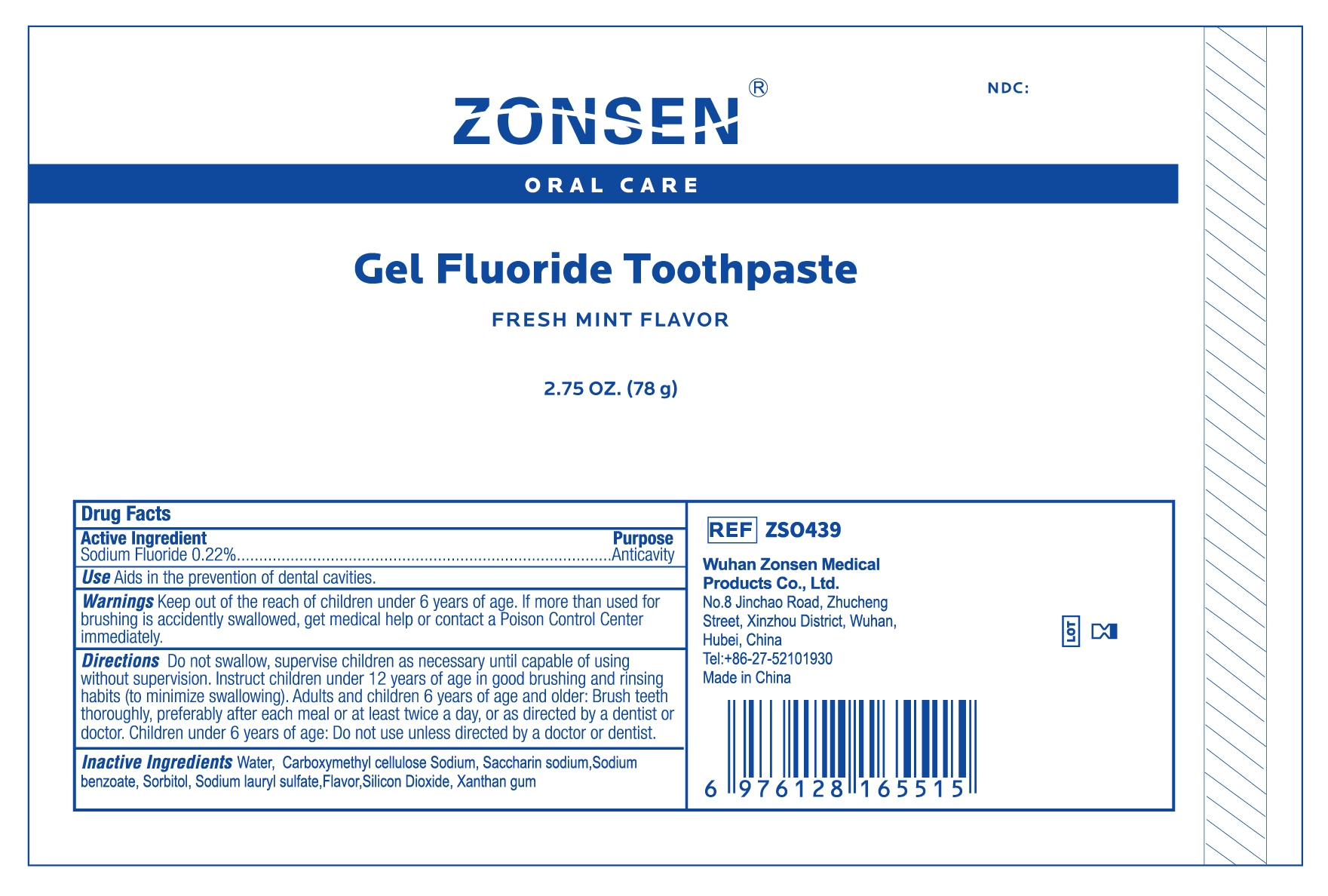 DRUG LABEL: ZONSEN Gel Fluoride
NDC: 72932-015 | Form: GEL, DENTIFRICE
Manufacturer: Wuhan Zonsen Medical Products Co., Ltd.
Category: otc | Type: HUMAN OTC DRUG LABEL
Date: 20250211

ACTIVE INGREDIENTS: SODIUM FLUORIDE 0.22 g/100 g
INACTIVE INGREDIENTS: SODIUM LAURYL SULFATE; XANTHAN GUM; SACCHARIN SODIUM; SORBITOL; SODIUM BENZOATE; WATER; SILICON DIOXIDE; CARBOXYMETHYLCELLULOSE SODIUM

ACTIVE INGREDIENT

Sodium Fluoride 0.22%

PURPOSE

Anticavity

INDICATIONS AND USAGE

Aids in the prevention of dental cavities.

WARNINGS

Keep out of the reach of children under 6 years of age. If more than used for brushing is accidently swallowed, get medical help or contact a Poison Control Center immediately.

DOSAGE AND ADMINISTRATION

Do not swallow, supervise children as necessary until capable of using without supervision. Instruct Children under 12 years of age in good brushing and rinsing habits (to minimize swallowing). Adults and children 6 years of age and older: Brush teeth thoroughly, preferably after each meal or at least twice a day, or as directed by a dentist or doctor. Children under 6 years of age: Do not use unless directed by a doctor or dentist.

INACTIVE INGREDIENT

Water, Carboxymethyl cellulose Sodium, Saccharin sodium,Sodium benzoate, Sorbitol, Sodium lauryl sulfate,Flavor,Silicon Dioxide, Xanthan gum

KEEP OUT OF REACH OF CHILDREN

Keep out of the reach of children under 6 years of age. If more than used for brushing is accidently swallowed, get medical help or contact a Poison Control Center immediately.

PACKAGE LABEL

ZONSEN NDC: 72932-015-00

Oral Care

Gel Fluoride Toothpaste

FRESH MINT FLAVOR

0.6 OZ. (17 g)

PACKAGE LABEL

ZONSEN NDC: 72932-015-01

Oral Care

Gel Fluoride Toothpaste

FRESH MINT FLAVOR

0.85 OZ. (24 g)

PACKAGE LABEL

ZONSEN NDC: 72932-015-02

Oral Care

Gel Fluoride Toothpaste

FRESH MINT FLAVOR

1.5 OZ. (43 g)

PACKAGE LABEL

ZONSEN NDC: 72932-015-03

Oral Care

Gel Fluoride Toothpaste

FRESH MINT FLAVOR

2.75 OZ. (78 g)